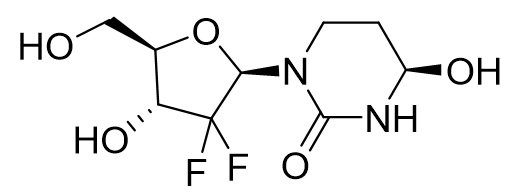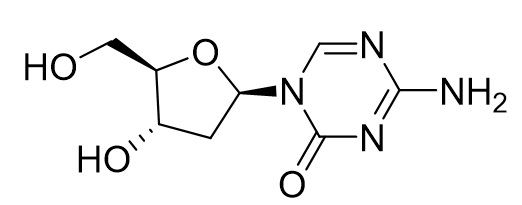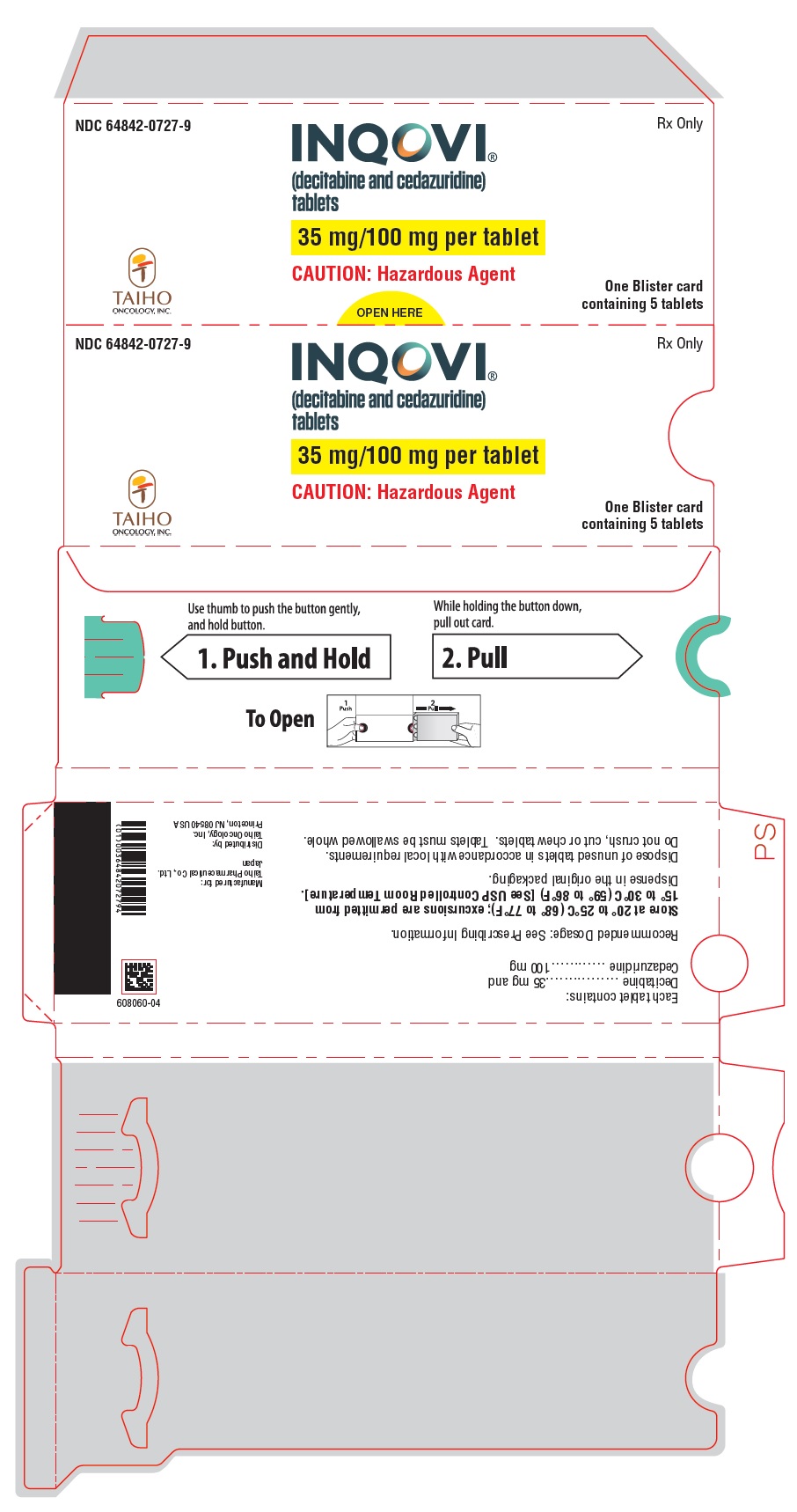 DRUG LABEL: INQOVI
NDC: 64842-0727 | Form: TABLET, FILM COATED
Manufacturer: Taiho Pharmaceutical Co., Ltd.
Category: prescription | Type: HUMAN PRESCRIPTION DRUG LABEL
Date: 20251208

ACTIVE INGREDIENTS: CEDAZURIDINE 100 mg/1 1; DECITABINE 35 mg/1 1
INACTIVE INGREDIENTS: LACTOSE MONOHYDRATE; HYPROMELLOSE, UNSPECIFIED; CROSCARMELLOSE SODIUM; SILICON DIOXIDE; MAGNESIUM STEARATE; POLYVINYL ALCOHOL, UNSPECIFIED; TITANIUM DIOXIDE; POLYETHYLENE GLYCOL, UNSPECIFIED; TALC; FERRIC OXIDE RED

HIGHLIGHTS OF PRESCRIBING INFORMATION

These highlights do not include all the information needed to use INQOVI safely and effectively. See full prescribing information for INQOVI.
INQOVI® (decitabine and cedazuridine) tablets, for oral use
Initial U.S. Approval: 2020

1 INDICATIONS AND USAGE

INQOVI is a combination of decitabine, a nucleoside metabolic inhibitor, and cedazuridine, a cytidine deaminase inhibitor, indicated for treatment of adult patients with myelodysplastic syndromes (MDS), including previously treated and untreated, de novo and secondary MDS with the following French-American-British subtypes (refractory anemia, refractory anemia with ringed sideroblasts, refractory anemia with excess blasts, and chronic myelomonocytic leukemia [CMML]) and intermediate-1, intermediate-2, and high-risk International Prognostic Scoring System groups. (1)

2 DOSAGE AND ADMINISTRATION

- The recommended dosage of INQOVI is 1 tablet (35 mg decitabine and 100 mg cedazuridine) taken orally once daily on Days 1 through 5 of each 28-day cycle. (2.2)
- Take INQOVI on an empty stomach. (2.2)

3 DOSAGE FORMS AND STRENGTHS

Tablets: 35 mg decitabine and 100 mg cedazuridine. (3)

4 CONTRAINDICATIONS

None. (4)

5 WARNINGS AND PRECAUTIONS

- Myelosuppression: Fatal and serious myelosuppression and infectious complications can occur. Obtain complete blood cell counts prior to initiation of INQOVI, prior to each cycle, and as clinically indicated to monitor for response and toxicity. Delay the next cycle and resume at the same or reduced dose as recommended. (2.3, 5.1)
- Embryo-Fetal Toxicity: Can cause fetal harm. Advise patients of reproductive potential of the potential risk to a fetus and to use effective contraception. (5.2, 8.1, 8.3)

6 ADVERSE REACTIONS

Most common adverse reactions (incidence ≥ 20%) are fatigue, constipation, hemorrhage, myalgia, mucositis, arthralgia, nausea, dyspnea, diarrhea, rash, dizziness, febrile neutropenia, edema, headache, cough, decreased appetite, upper respiratory tract infection, pneumonia, and transaminase increased. The most common Grade 3 or 4 laboratory abnormalities (≥ 50%) were leukocytes decreased, platelet count decreased, neutrophil count decreased, and hemoglobin decreased. (6.1)

To report SUSPECTED ADVERSE REACTIONS, contact Taiho Oncology, Inc. at 1-844-878-2446 or FDA at 1-800-FDA-1088 or www.fda.gov/medwatch.

7 DRUG INTERACTIONS

Drugs Metabolized by Cytidine Deaminase: Avoid coadministration with INQOVI. (7)

8 USE IN SPECIFIC POPULATIONS

- Lactation: Advise not to breastfeed. (8.2)
- Infertility: Can impair fertility. (8.3)

FULL PRESCRIBING INFORMATION

1 INDICATIONS AND USAGE

INQOVI is indicated for treatment of adult patients with myelodysplastic syndromes (MDS), including previously treated and untreated, de novo and secondary MDS with the following French-American-British subtypes (refractory anemia, refractory anemia with ringed sideroblasts, refractory anemia with excess blasts, and chronic myelomonocytic leukemia [CMML]) and intermediate-1, intermediate-2, and high-risk International Prognostic Scoring System groups.

2 DOSAGE AND ADMINISTRATION

2.1 Important Administration Information

Do NOT substitute INQOVI for an intravenous decitabine product within a cycle.

Consider administering antiemetics prior to each dose to minimize nausea and vomiting [see Adverse Reactions (6.1)].

2.2 Recommended Dosage

The recommended dosage of INQOVI is 1 tablet (containing 35 mg decitabine and 100 mg cedazuridine) orally once daily on Days 1 through 5 of each 28-day cycle for a minimum of 4 cycles until disease progression or unacceptable toxicity. A complete or partial response may take longer than 4 cycles.

Instruct patients of the following:

- Take INQOVI at the same time each day.
- Swallow tablets whole. Do not cut, crush, or chew tablets.
- Do not consume food 2 hours before and 2 hours after each dose.
- Take one tablet a day for 5 days in each cycle. If the patient misses a dose within 12 hours of the time it is usually taken, instruct patients to take the missed dose as soon as possible and then to resume the normal daily dosing schedule. Extend the dosing period by one day for every missed dose to complete 5 daily doses for each cycle.
- Do not take an additional dose if vomiting occurs after INQOVI administration but continue with the next schedule dose.

INQOVI is a hazardous drug. Follow applicable special handling and disposal procedures.^1

2.3 Monitoring and Dosage Modifications for Adverse Reactions

Hematologic Adverse Reactions

Obtain complete blood cell counts prior to initiating INQOVI and before each cycle. Delay the next cycle if absolute neutrophil count (ANC) is less than 1,000/μL and platelets are less than 50,000/μL in the absence of active disease. Monitor complete blood cell counts until ANC is 1,000/μL or greater and platelets are 50,000/μL or greater [see Warnings and Precautions (5.1)].

- If hematologic recovery occurs (ANC at least 1,000/μL and platelets at least 50,000/μL) within 2 weeks of achieving remission, continue INQOVI at the same dose.
- If hematologic recovery does not occur (ANC at least 1,000/μL and platelets at least 50,000/μL) within 2 weeks of achieving remission,
  - Delay INQOVI for up to 2 additional weeks AND
  - Resume at a reduced dose by administering INQOVI on Days 1 through 4. Consider further dose reductions in the order listed in Table 1 if myelosuppression persists after a dose reduction. Maintain or increase dose in subsequent cycles as clinically indicated.

Table 1: Recommended INQOVI Dose Reductions for Myelosuppression
Dose Reduction | Dosage
First | 1 tablet orally once daily on Days 1 through 4
Second | 1 tablet orally once daily on Days 1 through 3
Third | 1 tablet orally once daily on Days 1, 3 and 5

Manage persistent severe neutropenia and febrile neutropenia with supportive treatment [see Warnings and Precautions (5.1)].

Non-Hematologic Adverse Reactions

Delay the next cycle for the following non-hematologic adverse reactions and resume at the same or reduced dose upon resolution:

- Serum creatinine 2 mg/dL or greater
- Serum bilirubin 2 times upper limit of normal (ULN) or greater
- Aspartate aminotransferase (AST) or alanine aminotransferase (ALT) 2 times ULN or greater
- Active or uncontrolled infection

3 DOSAGE FORMS AND STRENGTHS

INQOVI tablets contain 35 mg decitabine and 100 mg cedazuridine. The tablets are biconvex, oval-shaped, film-coated, red and debossed with “H35” on one side.

4 CONTRAINDICATIONS

None.

5 WARNINGS AND PRECAUTIONS

5.1 Myelosuppression

Fatal and serious myelosuppression can occur with INQOVI. Based on laboratory values, new or worsening thrombocytopenia occurred in 82% of patients, with Grade 3 or 4 occurring in 76%. Neutropenia occurred in 73% of patients, with Grade 3 or 4 occurring in 71%. Anemia occurred in 71% of patients, with Grade 3 or 4 occurring in 55%. Febrile neutropenia occurred in 33% of patients, with Grade 3 or 4 occurring in 32%. Myelosuppression (thrombocytopenia, neutropenia, anemia, and febrile neutropenia) is the most frequent cause of INQOVI dose reduction or interruption, occurring in 36% of patients. Permanent discontinuation due to myelosuppression (febrile neutropenia) occurred in 1% of patients. Myelosuppression and worsening neutropenia may occur more frequently in the first or second treatment cycles and may not necessarily indicate progression of underlying MDS.

Fatal and serious infectious complications can occur with INQOVI. Pneumonia occurred in 21% of patients, with Grade 3 or 4 occurring in 15%. Sepsis occurred in 14% of patients, with Grade 3 or 4 occurring in 11%. Fatal pneumonia occurred in 1% of patients, fatal sepsis in 1%, and fatal septic shock in 1% [see Adverse Reactions (6.1)].

Obtain complete blood cell counts prior to initiation of INQOVI, prior to each cycle, and as clinically indicated to monitor response and toxicity. Administer growth factors and anti-infective therapies for treatment or prophylaxis as appropriate. Delay the next cycle and resume at the same or reduced dose as recommended [see Dosage and Administration (2.3)].

5.2 Embryo-Fetal Toxicity

Based on findings from human data, animal studies, and its mechanism of action, INQOVI can cause fetal harm when administered to a pregnant woman. In nonclinical studies with decitabine in mice and rats, decitabine was teratogenic, fetotoxic, and embryotoxic at doses less than the recommended human dose.

Advise pregnant women of the potential risk to a fetus. Advise females of reproductive potential to use effective contraception during treatment with INQOVI and for 6 months after the last dose. Advise males with female partners of reproductive potential to use effective contraception during treatment with INQOVI and for 3 months after the last dose [see Use in Specific Populations (8.1, 8.3)].

6 ADVERSE REACTIONS

The following clinically significant adverse reactions are described elsewhere in the labeling:

- Myelosuppression [see Warnings and Precautions (5.1)]

6.1 Clinical Trials Experience

Because clinical trials are conducted under widely variable conditions, adverse event rates observed in clinical trials of a drug cannot be directly compared with rates of clinical trials of another drug and may not reflect the rates observed in practice.

Myelodysplastic Syndrome and Chronic Myelomonocytic Leukemia

The safety of INQOVI was evaluated in a pooled safety population that includes patients enrolled in Study ASTX727-01-B and Study ASTX727-02 [see Clinical Studies (14)].

Patients were randomized to receive INQOVI (35 mg decitabine and 100 mg cedazuridine) orally once daily on Days 1 through 5 in Cycle 1 and decitabine 20 mg/m^2 intravenously on Days 1 through 5 in Cycle 2, or the reverse sequence, and then INQOVI (35 mg decitabine and 100 mg cedazuridine) orally once daily on Days 1 through 5 of each 28-day cycle in Cycles 3 and beyond. Patients were allowed to have one prior cycle of decitabine or azacitidine and there was no limit for body weight or surface area. Among the patients who received INQOVI, 61% of patients were exposed for 6 months or longer and 24% were exposed to INQOVI for greater than 1 year.

Serious adverse reactions occurred in 68% of patients who received INQOVI. Serious adverse reactions in > 5% of patients included febrile neutropenia (30%), pneumonia (14%), and sepsis (13%). Fatal adverse reactions occurred in 6% of patients. These included sepsis (1%), septic shock (1%), pneumonia (1%), respiratory failure (1%), and one case each of cerebral hemorrhage and sudden death.

Permanent discontinuation due to an adverse reaction occurred in 5% of patients who received INQOVI. The most frequent adverse reactions resulting in permanent discontinuation were febrile neutropenia (1%) and pneumonia (1%).

Dose interruptions due to an adverse reaction occurred in 41% of patients who received INQOVI. Adverse reactions requiring dosage interruptions in > 5% of patients who received INQOVI included neutropenia (18%), febrile neutropenia (8%), thrombocytopenia (6%), and anemia (5%).

Dose reductions due to an adverse reaction occurred in 19% of patients who received INQOVI. Adverse reactions requiring dosage reductions in > 2% of patients who received INQOVI included neutropenia (12%), anemia (3%), and thrombocytopenia (3%).

The most common adverse reactions (≥ 20%) were fatigue, constipation, hemorrhage, myalgia, mucositis, arthralgia, nausea, dyspnea, diarrhea, rash, dizziness, febrile neutropenia, edema, headache, cough, decreased appetite, upper respiratory tract infection, pneumonia, and transaminase increased. The most common Grade 3 or 4 laboratory abnormalities (≥ 50%) were leukocytes decreased, platelet count decreased, neutrophil count decreased, and hemoglobin decreased.

Table 2 summarizes the adverse reactions in the pooled safety population.

Table 2: Adverse Reactions (≥ 10%) in Patients Who Received INQOVI in Pooled Safety Population
Adverse Reactions | INQOVI Cycle 1 N=107 |  | Intravenous Decitabine Cycle 1 N=106 |  | INQOVI [Includes adverse reactions that occurred during all cycles, including during treatment with 1 cycle of intravenous decitabine.] All Cycles N=208
Adverse Reactions | All Grades (%) | Grades 3-4 (%) | All Grades (%) | Grades 3-4 (%) | All Grades (%) | Grades 3-4 (%)
General disorders and administration site conditions
Fatigue [Includes fatigue, asthenia, and lethargy] | 29 | 2 | 25 | 0 | 55 | 5
Hemorrhage [Includes contusion, epistaxis, petechiae, hematuria, conjunctival hemorrhage, mouth hemorrhage, purpura, angina bullosa hemorrhagica, gingival bleeding, hematoma, hemoptysis, eye contusion, hemorrhagic diathesis, increased tendency to bruise, vaginal hemorrhage, abdominal wall hematoma, blood blister, bone contusion, catheter site bruise, ecchymosis, genital hemorrhage, intra-abdominal hematoma, oral mucosa hematoma, periorbital hemorrhage, procedural hemorrhage, pulmonary alveolar hemorrhage, retinal hemorrhage, scleral hemorrhage, thrombotic thrombocytopenic purpura, tongue hemorrhage, and vessel puncture site hemorrhage] | 24 | 2 | 17 | 0 | 43 | 3
Edema [Includes edema peripheral, peripheral swelling, swelling face, fluid overload, localized edema, face edema, edema, eye swelling, eyelid edema, fluid retention, periorbital swelling, scrotal edema, scrotal swelling, and swelling] | 10 | 0 | 11 | 0 | 30 | 0.5
Pyrexia | 7 | 0 | 7 | 0 | 19 | 1
Gastrointestinal disorders
Constipation [Includes constipation and feces hard] | 20 | 0 | 23 | 0 | 44 | 0
Mucositis [Includes oropharyngeal pain, stomatitis, mouth ulceration, proctalgia, oral pain, gingivitis, oral disorder, gingival pain, colitis, glossodynia, mouth swelling, pharyngitis, proctitis, duodenitis, enteritis, gingival discomfort, gingival swelling, lip disorder, lip ulceration, mucosal ulceration, nasal ulcer, noninfective gingivitis, oral mucosal blistering, oral mucosal erythema, pharyngeal erythema, pharyngeal ulceration, tongue ulceration, and vulvitis] | 18 | 1 | 24 | 2 | 41 | 4
Nausea | 25 | 0 | 16 | 0 | 40 | 0.5
Diarrhea [Includes diarrhea and feces soft] | 16 | 0 | 11 | 0 | 37 | 1
Transaminase increased [Includes alanine aminotransferase increased, aspartate aminotransferase increased, blood alkaline phosphatase increased, gamma-glutamyltransferase increased, liver function test increased, and transaminases increased] | 12 | 1 | 3 | 0 | 21 | 3
Abdominal pain [Includes abdominal pain, abdominal pain upper, abdominal pain lower, epigastric discomfort, and abdominal discomfort] | 9 | 0 | 7 | 0 | 19 | 1
Vomiting | 5 | 0 | 5 | 0 | 15 | 0
Musculoskeletal and connective tissue disorders
Myalgia [Includes myalgia, pain in extremity, muscle spasms, pain, musculoskeletal pain, non-cardiac chest pain, muscular weakness, musculoskeletal chest pain, flank pain, musculoskeletal stiffness, muscle strain, and musculoskeletal discomfort] | 9 | 2 | 16 | 1 | 42 | 3
Arthralgia [Includes arthralgia, back pain, neck pain, joint stiffness, pain in jaw, joint swelling, bursitis, joint range of motion decreased, and joint injury] | 9 | 1 | 13 | 1 | 40 | 3
Respiratory, thoracic, and mediastinal disorders
Dyspnea [Includes dyspnea, dyspnea exertional, hypoxia, wheezing, chronic obstructive pulmonary disease, and tachypnoea] | 17 | 3 | 9 | 3 | 38 | 6
Cough [Includes cough and productive cough] | 7 | 0 | 8 | 0 | 28 | 0
Blood & lymphatic system disorders
Febrile neutropenia | 10 | 10 | 13 | 13 | 33 | 32
Skin and subcutaneous tissue disorders
Rash [Includes maculo-papular rash, rash, erythema, skin lesion, folliculitis, dermatitis, dermatitis acneiform, eczema, erythema multiforme, rash erythematous, seborrheic keratosis, skin ulcer, dermatitis allergic, dermatitis contact, eczema nummular, genital erythema, rash papular, rash pruritic, rash pustular, seborrheic dermatitis, skin exfoliation, skin irritation, stasis dermatitis, and ulcerative keratitis] | 12 | 1 | 11 | 1 | 33 | 0.5
Nervous system disorders
Dizziness [Includes dizziness, vertigo, postural dizziness, and positional vertigo] | 16 | 1 | 11 | 0 | 33 | 2
Headache [Includes headache, sinus pain, and sinus headache] | 22 | 0 | 13 | 0 | 30 | 0
Neuropathy [Includes hypoesthesia, paresthesia, neuropathy peripheral, gait disturbance, peripheral sensory neuropathy, ataxia, balance disorder, brachial plexopathy, carpal tunnel syndrome, and radicular pain] | 4 | 0 | 8 | 0 | 13 | 0
Metabolism and nutritional disorders
Decreased appetite | 10 | 1 | 6 | 0 | 24 | 2
Infections and infestations
Upper respiratory tract infection [Includes upper respiratory tract infection, nasopharyngitis, sinusitis, and viral upper respiratory tract infection] | 6 | 0 | 3 | 0 | 23 | 1
Pneumonia [Includes pneumonia, pneumonitis, atypical pneumonia, and lung infection] | 7 | 7 | 7 | 5 | 21 | 15
Sepsis [Includes sepsis, bacteremia, septic shock, endocarditis, pseudomonal bacteremia, and staphylococcal bacteremia] | 6 | 6 | 2 | 1 | 14 | 11
Cellulitis [Includes cellulitis, catheter site cellulitis, and infected bite] | 4 | 1 | 3 | 2 | 12 | 5
Investigations
Renal impairment [Includes blood creatinine increased, acute kidney injury, blood urea increased, blood creatine increased, and renal failure] | 9 | 0 | 8 | 1 | 18 | 0
Weight decreased | 5 | 0 | 3 | 0 | 10 | 1
Injury, poisoning, and procedural complications
Fall | 4 | 0 | 1 | 0 | 12 | 1
Psychiatric disorders
Insomnia | 6 | 0 | 2 | 0 | 12 | 0.5
Vascular disorders
Hypotension [Includes hypotension, blood pressure decreased, and cardiogenic shock] | 4 | 0 | 6 | 1 | 11 | 2
Cardiac Disorders
Arrhythmia [Includes sinus tachycardia, atrial fibrillation, bradycardia, tachycardia, atrial flutter, sinus bradycardia, and conduction disorder] | 3 | 0 | 2 | 0 | 11 | 1

Clinically relevant adverse reactions in < 10% of patients who received INQOVI included:

- Acute febrile neutrophilic dermatosis (Sweet’s syndrome) (1%)
- Tumor lysis syndrome (0.5%)

Table 3: Select Laboratory Abnormalities (> 20%) Worsening from Baseline in Patients Who Received INQOVI in Pooled Safety Population
Lab Abnormality [Includes any lab abnormalities that worsened by one or more grades. Grade 3-4 includes any lab abnormalities that worsened to Grade 3 or Grade 4.] | INQOVI Cycle 1 [The denominator used to calculate the rate varied from 103 to 107 for INQOVI Cycle 1, from 102 to 106 for Intravenous Decitabine Cycle and from 203 to 208 for INQOVI All Cycles based on the number of patients with a baseline value and at least one post-treatment value.] |  | Intravenous Decitabine Cycle 1 |  | INQOVI All Cycles
Lab Abnormality [Includes any lab abnormalities that worsened by one or more grades. Grade 3-4 includes any lab abnormalities that worsened to Grade 3 or Grade 4.] | All Grades (%) | Grades 3-4 (%) | All Grades (%) | Grades 3-4 (%) | All Grades (%) | Grades 3-4 (%)
Hematology
Leukocytes decreased | 79 | 65 | 77 | 59 | 87 | 81
Platelet count decreased | 79 | 65 | 77 | 67 | 82 | 76
Neutrophil count decreased | 70 | 65 | 62 | 59 | 73 | 71
Hemoglobin decreased | 58 | 41 | 59 | 36 | 71 | 55
Chemistry
Glucose increased | 19 | 0 | 11 | 0 | 54 | 7
Albumin decreased | 22 | 1 | 20 | 0 | 45 | 2
Alkaline phosphatase increased | 22 | 1 | 12 | 0 | 42 | 0.5
Glucose decreased | 14 | 0 | 17 | 0 | 40 | 1
Alanine aminotransferase increased | 13 | 1 | 7 | 0 | 37 | 2
Sodium decreased | 9 | 2 | 8 | 0 | 30 | 4
Calcium decreased | 16 | 0 | 12 | 0 | 30 | 2
Aspartate aminotransferase increased | 6 | 1 | 2 | 0 | 30 | 2
Creatinine increased | 7 | 0 | 8 | 0 | 29 | 0.5

6.2 Postmarketing Experience

The following adverse reactions have been identified during postapproval use of intravenous decitabine. Because these reactions are reported voluntarily from a population of uncertain size, it is not always possible to reliably estimate their frequency or establish a causal relationship to drug exposure.

Blood and Lymphatic System Disorders: Differentiation syndrome

Respiratory, Thoracic and Mediastinal Disorders: Interstitial lung disease

Cardiac Disorders: Cardiomyopathy

7 DRUG INTERACTIONS

7.1 Effects of INQOVI on Other Drugs

Drugs Metabolized by Cytidine Deaminase

Cedazuridine is an inhibitor of the cytidine deaminase (CDA) enzyme. Coadministration of INQOVI with drugs that are metabolized by CDA may result in increased systemic exposure with potential for increased toxicity of these drugs [see Clinical Pharmacology (12.3)]. Avoid coadministration of INQOVI with drugs that are metabolized by CDA.

8 USE IN SPECIFIC POPULATIONS

8.1 Pregnancy

Risk Summary

Based on findings from human data, animal studies, and its mechanism of action [see Clinical Pharmacology (12.1)], INQOVI can cause fetal harm when administered to a pregnant woman. A single published case report of intravenous decitabine use throughout the first trimester during pregnancy describes adverse developmental outcomes, including major birth defects (structural abnormalities). In animal reproduction studies, intravenous administration of decitabine to pregnant mice and rats during organogenesis at doses approximately 7% of the recommended human dose on a body surface area (mg/m^2) basis caused adverse developmental outcomes, including increased embryo-fetal mortality, alterations to growth, and structural abnormalities (see Data). Advise pregnant women of the potential risk to a fetus.

The estimated background risk of major birth defects and miscarriage for the indicated population is unknown. All pregnancies have a background risk of birth defect, loss, or other adverse outcomes. In the U.S. general population, the estimated background risk of major birth defects and miscarriage in clinically recognized pregnancies is 2% to 4% and 15% to 20%, respectively.

Data

Human Data

There are no available data on INQOVI use in pregnant women.

A single published case report of intravenous decitabine pregnancy exposure in a 39-year-old woman with a hematologic malignancy described multiple structural abnormalities after 6 cycles of therapy in the 18th week of gestation. These abnormalities included holoprosencephaly, absence of nasal bone, mid-facial deformity, cleft lip and palate, polydactyly, and rocker-bottom feet. The pregnancy was terminated.

Animal Data

No reproductive or developmental toxicity studies have been conducted with INQOVI or cedazuridine.

In utero exposure to decitabine causes temporal-related defects in the rat and/or mouse, which include growth suppression, exencephaly, defective skull bones, rib/sternabrae defects, phocomelia, digit defects, micrognathia, gastroschisis, and micromelia. Decitabine inhibits proliferation and increases apoptosis of neural progenitor cells of the fetal central nervous system (CNS) and induces palatal clefting in the developing murine fetus. Studies in mice have also shown that decitabine administration during osteoblastogenesis (Day 10 of gestation) induces bone loss in offspring.

In mice exposed to single intraperitoneal decitabine injections (0, 0.9 and 3.0 mg/m^2, approximately 2% and 7% of the recommended daily clinical dose, respectively) over gestation Days 8, 9, 10 or 11, no maternal toxicity was observed, but reduced fetal survival was observed after treatment at 3 mg/m^2 and decreased fetal weight was observed at both dose levels. The 3 mg/m^2 dose elicited characteristic fetal defects for each treatment day, including supernumerary ribs (both dose levels), fused vertebrae and ribs, cleft palate, vertebral defects, hind-limb defects, and digital defects of fore- and hind-limbs.

In rats given a single intraperitoneal injection of 2.4, 3.6 or 6 mg/m^2 decitabine (approximately 5, 8, or 13% the daily recommended clinical dose, respectively) on gestation Days 9-12, no maternal toxicity was observed. No live fetuses were seen at any dose when decitabine was injected on gestation Day 9. A significant decrease in fetal survival and reduced fetal weight at doses greater than 3.6 mg/m^2 was seen when decitabine was given on gestation Day 10. Increased incidences of vertebral and rib anomalies were seen at all dose levels, and induction of exophthalmia, exencephaly, and cleft palate were observed at 6.0 mg/m^2. Increased incidence of foredigit defects was seen in fetuses at doses greater than 3.6 mg/m^2. Reduced size and ossification of long bones of the fore-limb and hind-limb were noted at 6 mg/m^2.

The effect of decitabine on postnatal development and reproductive capacity was evaluated in mice administered a single 3 mg/m^2 intraperitoneal injection (approximately 7% the recommended daily clinical dose) on Day 10 of gestation. Body weights of males and females exposed in utero to decitabine were significantly reduced relative to controls at all postnatal time points. No consistent effect on fertility was seen when female mice exposed in utero were mated to untreated males. Untreated females mated to males exposed in utero showed decreased fertility at 3 and 5 months of age (36% and 0% pregnancy rate, respectively). Follow up studies indicated that treatment of pregnant mice with decitabine on gestation Day 10 was associated with a reduced pregnancy rate resulting from effects on sperm production in the F1-generation.

8.2 Lactation

Risk Summary

There are no data on the presence of cedazuridine, decitabine, or their metabolites in human milk or on their effects on the breastfed child or milk production. Because of the potential for serious adverse reactions in the breastfed child, advise women not to breastfeed during treatment with INQOVI and for 2 weeks after the last dose.

8.3 Females and Males of Reproductive Potential

INQOVI can cause fetal harm when administered to a pregnant woman [see Use in Specific Populations (8.1)].

Pregnancy Testing

Verify the pregnancy status in females of reproductive potential prior to initiating INQOVI.

Contraception

Females

Advise females of reproductive potential to use effective contraception during treatment with INQOVI and for 6 months after the last dose.

Males

Based on genotoxicity findings, advise males with female partners of reproductive potential to use effective contraception during treatment with INQOVI and for 3 months after the last dose [see Nonclinical Toxicology (13.1)].

Infertility

Based on findings of decitabine and cedazuridine in animals, INQOVI may impair male fertility [see Nonclinical Toxicology (13.1)]. The reversibility of the effect on fertility is unknown.

8.4 Pediatric Use

The safety and effectiveness of INQOVI have not been established in pediatric patients.

8.5 Geriatric Use

Of the 208 patients in clinical studies who received INQOVI, 75% were age 65 years and older, while 36% were age 75 years and older. No overall differences in safety or effectiveness were observed between patients age 65 years and older, 75 years and older, and younger patients.

8.6 Renal Impairment

No dosage modification of INQOVI is recommended for patients with mild or moderate renal impairment (creatinine clearance [CLcr] of 30 to 89 mL/min based on Cockcroft-Gault). Due to the potential for increased adverse reactions, monitor patients with moderate renal impairment (CLcr 30 to 59 mL/min) frequently for adverse reactions. INQOVI has not been studied in patients with severe renal impairment (CLcr 15 to 29 mL/min) or end-stage renal disease (ESRD: CLcr <15 mL/min) [see Clinical Pharmacology (12.3)].

11 DESCRIPTION

Decitabine

Decitabine is a nucleoside metabolic inhibitor. Decitabine is a white to off-white solid with the molecular formula of C8H12N4O4 and a molecular weight of 228.21 daltons. Its international union of pure and applied chemistry (IUPAC) chemical name is 4-amino-1-[(2R,4S,5R)-4-hydroxy-5-(hydroxymethyl)oxolan-2-yl]-1,3,5-triazin-2(1H)-one and it has the following structural formula:

Cedazuridine

Cedazuridine is a cytidine deaminase inhibitor. Cedazuridine is a white to off-white solid with the molecular formula of C9H14F2N2O5 and a molecular weight of 268.21 daltons. Its IUPAC chemical name is (4R)-1-[(2R,4R,5R)-3,3-difluoro-4-hydroxy-5-(hydroxymethyl)oxolan-2-yl]-4-hydroxy-1,3-diazinan-2-one and it has the following structural formula:

INQOVI

INQOVI (decitabine and cedazuridine) tablets, for oral use contain 35 mg decitabine and 100 mg cedazuridine. The tablets are biconvex, oval-shaped, film-coated, red and debossed with “H35” on one side. Each film-coated tablet contains the following inactive ingredients: lactose monohydrate, hypromellose, croscarmellose sodium, colloidal silicon dioxide, and magnesium stearate. The film coating material contains polyvinyl alcohol, titanium dioxide, polyethylene glycol, talc, and iron oxide red.

12 CLINICAL PHARMACOLOGY

12.1 Mechanism of Action

Decitabine is a nucleoside metabolic inhibitor that is believed to exert its effects after phosphorylation and direct incorporation into DNA and inhibition of DNA methyltransferase, causing hypomethylation of DNA and cellular differentiation and/or apoptosis. Decitabine inhibits DNA methylation in vitro, which is achieved at concentrations that do not cause major suppression of DNA synthesis. Decitabine-induced hypomethylation in cancer cells may restore normal function to genes that are critical for the control of cellular differentiation and proliferation. In rapidly dividing cells, the cytotoxicity of decitabine may also be attributed to the formation of covalent adducts between DNA methyltransferase and decitabine incorporated into DNA. Non-proliferating cells are relatively insensitive to decitabine.

Cytidine deaminase (CDA) is an enzyme that catalyzes the degradation of cytidine, including the cytidine analog decitabine. High levels of CDA in the gastrointestinal tract and liver degrade decitabine and limit its oral bioavailability. Cedazuridine is a CDA inhibitor. Administration of cedazuridine with decitabine increases systemic exposure of decitabine.

12.2 Pharmacodynamics

Decitabine induced hypomethylation both in vitro and in vivo. In patients administered the recommended dosage of INQOVI, the maximum change from baseline in the long interspersed nucleotide elements-1 (LINE-1) demethylation was observed at Day 8, with less than complete recovery of LINE-1 methylation to baseline at the end of the treatment cycle.

Based on the exposure-response analyses, a relationship between an increase in 5-day cumulative daily decitabine exposure and a greater likelihood of some adverse reactions (e.g., any grade neutropenias, thrombocytopenia) was observed in clinical studies.

12.3 Pharmacokinetics

The pharmacokinetics of decitabine and cedazuridine following administration of INQOVI at the recommended dosage in patients with MDS and CMML are shown in Table 4.

The geometric mean ratio (GMR) of decitabine area under the curve (AUC) following the first dose of INQOVI compared to that of intravenous decitabine on Day 1 was 60% (90% confidence intervals (CI): 55, 65) in patients with MDS and CMML [see Dosage and Administration (2.1)]. The GMR of decitabine AUC following 5 consecutive once daily doses of INQOVI compared to that of intravenous decitabine on Day 5 was 106% (90% CI: 98, 114) and the GMR of the 5-day cumulative decitabine AUC following 5 consecutive once daily doses of INQOVI compared to that of intravenous decitabine was 99% (90% CI: 93, 106).

An approximately dose-proportional increase in peak concentrations (Cmax) and AUC over the dosing interval was observed for decitabine following administration of oral decitabine at 20 mg to 40 mg once daily (0.6 to 1.1 times the recommended dose) in combination with 100 mg oral cedazuridine, and for cedazuridine following administration of oral cedazuridine at 40 to 100 mg once daily (0.4 to 1.0 times the recommended dose) in combination with 20 mg oral decitabine.

Table 4: Pharmacokinetics of the Components of INQOVI [Mean (%CV)]
Parameter | Decitabine | Cedazuridine
General Information
With the recommended dosage of INQOVI for 5 consecutive days:
5-day cumulative AUC, ng.hr/mL | 851 (50%) | --
Day 1 AUC, ng·hr/mL | 103 (55%) | 2950 (49%)
Steady state AUC, ng·hr/mL | 178 (53%) | 3291 (45%)
Time to steady state, days | 2 | 2
Accumulation ratio based on AUC | 1.7 (42%) | 1.1 (63%)
Cmax, ng/mL | 145 (55%) | 371 (52%)
Absorption
Bioavailability | Cedazuridine increases oral decitabine exposure | 20% (23%)
Tmax, hours [Median (range)] | 1 (0.3 to 3.0) | 3 (1.5 to 6.1)
Distribution
V/F at steady state, L | 417 (54%) | 296 (51%)
Fraction unbound, in vitro | 96% (4%) to 94% (2%) between 17 ng/mL to 342 ng/mL | 66% (6%) to 62% (2%) between 1000 ng/mL and 50000 ng/mL
Elimination
Half-life at steady state [Mean (SD)] , hours | 1.5 (27%) | 6.7 (19%)
CL/F at steady state, L/hours | 197 (53%) | 30.3 (46%)
Metabolism
Primary Pathways | Primarily by cytidine deaminase (CDA) and by physicochemical degradation | Conversion to epimer by physicochemical degradation
Excretion [Healthy subjects]
Total (% unchanged) | -- | 46% (21%) in urine and 51% (27%) in feces
Cmax= maximum plasma concentration; AUC0-24h=area under the plasma concentration-time curve from time zero to 24 hours; CV=coefficient of variation; SD=standard deviation; Tmax= Time to maximum concentration; V/F=apparent volume of distribution; CL/F=apparent clearance

Specific Populations

Age (32 to 90 years), sex, and mild hepatic impairment (total bilirubin > 1 to 1.5 × ULN or AST > ULN) did not have an effect on the pharmacokinetics of decitabine or cedazuridine after dosing with INQOVI.

Decitabine exposure (AUC) increased with decreasing body surface area or body weight, and cedazuridine exposure increased with decreasing CLcr; however, body surface area (1.3 to 2.9 m^2), body weight (41 to 158 kg), and mild to moderate renal impairment (CLcr 30 to 89 mL/min based on Cockcroft Gault) did not have a clinically meaningful effect on the pharmacokinetics of decitabine and cedazuridine after dosing with INQOVI.

The effects of moderate (total bilirubin > 1.5 to 3 × ULN and any AST) and severe hepatic impairment (total bilirubin > 3 × ULN and any AST) or severe renal impairment (CLcr 15 to <30 mL/min) and ESRD (CLcr <15 mL/min) on the pharmacokinetics of decitabine and cedazuridine are unknown.

Drug Interaction Studies

Clinical Studies

Decitabine had no clinically meaningful effect on the pharmacokinetics of cedazuridine. Cedazuridine increased the exposure of decitabine.

The coadministration of INQOVI with proton pump inhibitors had no clinically meaningful effect on exposure to decitabine or cedazuridine.

In vitro Studies

CYP Enzymes: Cedazuridine is not a substrate of cytochrome P450 (CYP) enzymes. Cedazuridine does not induce CYP1A, CYP2B6, CYP2C9, or CYP3A or inhibit CYP1A, CYP2B6, CYP2C8, CYP2C9, CYP2C19, CYP2D6, CYP2E1, or CYP3A.

Transporter Systems: Cedazuridine is not a substrate of P-glycoprotein (P-gp), MATE1, MATE2-K, OAT1, OAT3, OATP1B1, OAPT1B3, OATP2B1, OCT1, or OCT2, and does not inhibit P-gp, BCRP, MATE1, MATE2-K, OAT1, OAT3, OATP1B1, OATP1B3, or OCT2.

13 NONCLINICAL TOXICOLOGY

13.1 Carcinogenesis, Mutagenesis, Impairment of Fertility

Carcinogenicity studies with decitabine, cedazuridine, or their combination have not been conducted.

INQOVI is genotoxic. Decitabine increased mutation frequency in L5178Y mouse lymphoma cells, and mutations were produced in an E. coli lac-I transgene in colonic DNA of decitabine-treated mice. Decitabine also caused chromosomal rearrangements in larvae of fruit flies. Cedazuridine was genotoxic in a reverse bacterial mutation assay (Ames assay) and in an in vitro chromosomal aberration study using human lymphocytes.

Fertility and repeat-dose toxicity studies in animals showed adverse outcomes on reproductive function and fertility. In male mice given intraperitoneal injections of 0.15, 0.3, or 0.45 mg/m^2 decitabine (approximately 0.3% to 1% the recommended clinical dose) 3 times a week for 7 weeks, testes weights were reduced, abnormal histology was observed, and significant decreases in sperm number were found at doses ≥ 0.3 mg/m^2. In females mated to males dosed with ≥ 0.3 mg/m^2 decitabine, pregnancy rate was reduced, and preimplantation loss was significantly increased.

Decitabine was administered orally to rats at 0.75, 2.5, or 7.5 mg/kg/day in cycles of 5-days-on/23-days-off for a total of 90 days. Low testes and epididymis weights, abnormal histology, and reduced sperm number were observed at doses ≥ 0.75 mg/kg. The dose of 0.75 mg/kg resulted in exposures in animals that were approximately 3 times the exposure in patients at the recommended clinical dose based on AUC.

Cedazuridine was administered orally to mice at 100, 300, or 1,000 mg/kg/day in cycles of 7-days-on/21-days-off for a total of 91 days. Adverse findings in male and female reproductive organs were observed at the 1,000 mg/kg dose and included abnormal histology in the testes and epididymis, reduced sperm number, and abnormal histology in the ovary. The dose of 1,000 mg/kg/day resulted in exposures in animals that were approximately 108 times the exposure in patients at the recommended clinical dose. Adverse effects in male and female reproductive organs were reversible following a recovery period.

14 CLINICAL STUDIES

Study ASTX727-01-B

INQOVI was evaluated in Study ASTX727-01-B, an open-label, randomized, 2-cycle, 2-sequence crossover study (NCT02103478) that included 80 adult patients with MDS (International Prognostic Scoring System [IPSS] Intermediate-1, Intermediate-2, or high-risk) or CMML. Patients were randomized 1:1 to receive INQOVI (35 mg decitabine and 100 mg cedazuridine) orally in Cycle 1 and decitabine 20 mg/m^2 intravenously in Cycle 2 or the reverse sequence. Both INQOVI and intravenous decitabine were administered once daily on Days 1 through 5 of the 28-day cycle. Starting with Cycle 3, all patients received INQOVI orally once daily on Days 1 through 5 of each 28-day cycle until disease progression or unacceptable toxicity. Randomization was stratified by IPSS risk level. Twelve (15%) of the 80 patients went on to stem cell transplantation following INQOVI treatment.

The baseline demographic and disease characteristics are shown in Table 5.

Table 5: Demographics and Baseline Disease Characteristics for Study ASTX727-01-B
Characteristic | N=80
Age
Median (min, max) (years) | 71 (32, 90)
Sex (%)
Male | 76
Female | 24
Race (%)
White | 93
Black or African American | 3
Asian | 1
Other or Not Reported | 4
ECOG Performance Score (%)
0 | 44
1 | 48
2 | 9
Disease Category / IPSS (%)
MDS INT-1 | 44
MDS INT-2 | 24
MDS High-Risk | 11
CMML | 21
Prior HMA Therapy [One cycle only, per the Exclusion Criteria.] (%)
Prior Azacitidine | 4
Prior Decitabine | 4
Transfusion Dependence [Defined as documentation of ≥ 2 units of transfusion within 56 days prior to the first day of study treatment.] (%)
RBC Transfusion Dependence | 48
Platelet Transfusion Dependence | 15

Efficacy was established on the basis of complete response (CR) and the rate of conversion from transfusion dependence to transfusion independence. Efficacy results are shown in Table 6. The median follow-up time was 24.0 months (range: 12.0 to 28.8 months) and median treatment duration was 6.6 months (range < 0.1 to 27.9).

Table 6: Efficacy Results in Patients with MDS or CMML from Study ASTX727-01-B
Efficacy Endpoint | INQOVI N=80
Efficacy Endpoint | Complete Response (%) (95% CI) | 18 (10, 28)
Median Duration of CR - months (range) [From start of CR until relapse or death.] | 8.7 (1.1, 18.2)
Median Time to CR - months (range) | 4.8 (1.7, 10.0)

Among the 41 patients who were dependent on red blood cell (RBC) and/or platelet transfusions at baseline, 20 (49%) became independent of RBC and platelet transfusions during any consecutive 56-day post-baseline period. Of the 39 patients who were independent of both RBC and platelet transfusions at baseline, 25 (64%) remained transfusion-independent during any consecutive 56-day post-baseline period.

Study ASTX727-02

INQOVI was evaluated in ASTX727-02, an open-label, randomized, 2-cycle, 2-sequence crossover study (NCT03306264) that included 133 adult patients with MDS or CMML, including all French-American-British (FAB) classification criteria and IPSS Intermediate-1, Intermediate-2, or high-risk prognostic scores. Patients were randomized 1:1 to receive INQOVI (35 mg decitabine and 100 mg cedazuridine) orally in Cycle 1 and decitabine 20 mg/m^2 intravenously in Cycle 2 or the reverse sequence. Both INQOVI and intravenous decitabine were administered once daily on Days 1 through 5 of the 28-day cycle. Starting with Cycle 3, all patients received INQOVI orally once daily on Days 1 through 5 of each 28-day cycle until disease progression or unacceptable toxicity. No stratification was performed. Twenty-seven (20%) of the 133 patients went on to stem cell transplantation following INQOVI treatment.

The baseline demographic and disease characteristics are shown in Table 7.

Table 7: Demographics and Baseline Disease Characteristics for Study ASTX727-02
Characteristic | N=133
Age (years)
Median (min, max) | 71 (44, 88)
Sex (%)
Male | 65
Female | 35
Race (%)
White | 91
Black or African American | 3
Asian | 2
Other or Not Reported | 4
ECOG Performance Score (%)
0 | 41
1 | 59
Disease Category / IPSS (%)
MDS INT-1 | 44
MDS INT-2 | 20
MDS High Risk | 16
MDS Low Risk | 8
CMML | 12
Prior HMA Therapy [One cycle only, per the Exclusion Criteria.] (%)
Prior Azacitidine | 5
Prior Decitabine | 3
Transfusion Dependence [Defined as documentation of ≥ 2 units of transfusion within 56 days prior to the first day of study treatment.] (%)
RBC Transfusion Dependence | 39
Platelet Transfusion Dependence | 8

The primary outcome measure was comparison of the 5-day cumulative decitabine AUC between INQOVI and intravenous decitabine [see Clinical Pharmacology (12.3)]. Efficacy was established on the basis of complete response (CR) and the rate of conversion from transfusion dependence to transfusion independence. Efficacy results are shown in Table 8. The median follow-up time was 12.6 months (range: 9.3 to 20.5) and median treatment duration was 8.2 months (range 0.2 to 19.7).

Table 8: Efficacy Results in Patients with MDS or CMML from Study ASTX727-02
Efficacy Endpoints | INQOVI (N=133)
Efficacy Endpoints | Complete Response (%) (95% CI) | 21 (15, 29)
Median Duration of CR - months (range) [From start of CR until relapse or death.] | 7.5 (1.6, 17.5)
Median Time to CR - months (range) | 4.3 (2.1, 15.2)

Among the 57 patients who were dependent on RBC and/or platelet transfusions at baseline, 30 (53%) became independent of RBC and platelet transfusions during any 56-day post-baseline period. Of the 76 patients who were independent of both RBC and platelet transfusions at baseline, 48 (63%) remained transfusion-independent during any 56-day post-baseline period.

15 REFERENCES

1. OSHA Hazardous Drugs. OSHA. http://www.osha.gov/SLTC/hazardousdrugs/index.html

16 HOW SUPPLIED/STORAGE AND HANDLING

How Supplied

INQOVI tablets are biconvex, oval-shaped, film-coated, red, and debossed with “H35” on one side.

The tablets are packaged in blisters and supplied as follows:

- NDC: 64842-0727-9; 5 tablets in one blister card in a child-resistant carton

Storage and Handling

Store at 20°C to 25°C (68°F to 77°F); excursions permitted from 15°C to 30°C (59°F to 86°F) [see USP Controlled Room Temperature]. Dispense medication in the original packaging.

INQOVI is a hazardous drug. Follow applicable special handling and disposal procedures.^1

17 PATIENT COUNSELING INFORMATION

Advise the patient to read the FDA-approved patient labeling (Patient Information).

Myelosuppression

Advise patients of the risk of myelosuppression and to report any symptoms of fever, infection, anemia, or bleeding to their healthcare provider as soon as possible. Advise patients for the need for laboratory monitoring [see Warnings and Precautions (5.1)].

Embryo-Fetal Toxicity

Advise pregnant women of the potential risk to a fetus. Advise females of reproductive potential to inform their healthcare provider of a known or suspected pregnancy [see Warnings and Precautions (5.2), Use in Specific Populations (8.1)].

Advise females of reproductive potential to use effective contraception during treatment with INQOVI and for 6 months after the last dose [see Use in Specific Populations (8.3)].

Advise males with female partners of reproductive potential to use effective contraception during treatment with INQOVI and for 3 months after the last dose [see Use in Specific Populations (8.3), Nonclinical Toxicology (13.1)].

Lactation

Advise women not to breastfeed during treatment with INQOVI and for 2 weeks after the last dose [see Use in Specific Populations (8.2)].

Administration

Advise patients to take INQOVI at approximately the same time each day on an empty stomach. Instruct patients to avoid eating for at least 2 hours before and 2 hours after taking INQOVI. Advise patients on what to do when a dose is missed or vomited [see Dosage and Administration (2.2)].

Manufactured for:
Taiho Pharmaceutical Co., Ltd
Japan

Distributed by:
Taiho Oncology, Inc.
Princeton, NJ 08540 USA

PATIENT INFORMATION
INQOVI® (IN KOE' VEE)
(decitabine and cedazuridine)
tablets

What is INQOVI?

INQOVI is a prescription medicine used to treat adults with myelodysplastic syndromes (MDS), including chronic myelomonocytic leukemia (CMML). Your healthcare provider will determine if INQOVI can treat your type of MDS.

It is not known if INQOVI is safe or effective in children.

Before taking INQOVI, tell your healthcare provider about all of your medical conditions, including if you:

- have kidney problems
- have liver problems
- are pregnant or plan to become pregnant. INQOVI can harm your unborn baby. Tell your healthcare provider right away if you become pregnant or think you may be pregnant during treatment with INQOVI.
  Females who are able to become pregnant:
  - Your healthcare provider will check to see if you are pregnant before you start treatment with INQOVI.
  - You should use effective birth control during treatment with INQOVI and for at least 6 months after your last dose of INQOVI.
  Males with female partners who are able to become pregnant should use effective birth control during treatment with INQOVI and for 3 months after the last dose. Talk to your healthcare provider if you have questions about birth control options that are right for you.
- are breastfeeding or plan to breastfeed. It is not known if INQOVI passes into breast milk. Do not breastfeed during treatment with INQOVI and for 2 weeks after your last dose of INQOVI.

Tell your healthcare provider about all the medicines you take, including prescription and over-the-counter medicines, vitamins, and herbal supplements. Know the medicines you take. Keep a list of them to show your healthcare provider and pharmacist when you get a new medicine.

How should I take INQOVI?

- Take INQOVI exactly as your healthcare provider tells you to.
- Do not change your dose or stop taking INQOVI unless your healthcare provider tells you to.
- Your healthcare provider may tell you to decrease your dose, temporarily stop, or completely stop taking INQOVI if you get certain side effects.
- Take INQOVI one time a day at about the same time each day.
- Take INQOVI on an empty stomach. Do not eat for at least 2 hours before and 2 hours after taking INQOVI.
- Swallow INQOVI tablets whole. Do not cut, crush, or chew the tablet.
- If you miss a dose of INQOVI, take your dose as soon as possible if it is within 12 hours of your usual time. Then, continue taking INQOVI at your scheduled time. If you missed a dose by more than 12 hours, do not take additional doses to make up for the missed dose. Take your next scheduled dose on the following day at your usual time.
- If you vomit after taking a dose of INQOVI, do not take an additional dose. Take your next scheduled dose at your usual time.

What are the possible side effects of INQOVI?

INQOVI may cause serious side effects, including:

- Low blood cell counts. Low blood counts (white blood cells, platelets, and red blood cells) are common with INQOVI but can also be serious and lead to infections that may be life-threatening. If your blood cell counts are too low, your healthcare provider may need to delay treatment with INQOVI, lower your dose of INQOVI, or in some cases give you a medicine to help treat low blood cell counts. Your healthcare provider may need to give you antibiotic medicines to prevent or treat infections or fever while your blood cell counts are low. Your healthcare provider will check your blood cell counts before you start treatment and regularly during treatment with INQOVI. Call your healthcare provider right away if you get any of the following signs and symptoms of infection during treatment with INQOVI:

- fever
- chills

- body aches
- bruising more easily than usual

The most common side effects of INQOVI include:

- low white blood cell count (leukopenia)
- low platelets in your blood (thrombocytopenia)
- low white blood cell count (neutropenia)
- low red blood cell count (anemia)
- tiredness
- constipation
- bleeding
- muscle pain
- pain or sores in your mouth or throat
- joint pain
- nausea
- shortness of breath

- diarrhea
- rash
- dizziness
- fever with low white blood cell count (febrile neutropenia)
- swelling of arms or legs
- headache
- cough
- decreased appetite
- upper respiratory tract infection
- pneumonia
- changes in liver function tests

INQOVI may affect fertility in men. Talk to your healthcare provider if this is a concern for you.
These are not all of the possible side effects of INQOVI. Call your doctor for medical advice about side effects. You may report side effects to FDA at 1-800-FDA-1088.

How should I store INQOVI?

- Store INQOVI at room temperature between 68°F and 77°F (20°C and 25°C).
- Do not store INQOVI outside of the original blisters.
- Talk to your healthcare provider about how to safely throw away (dispose of) INQOVI.

Keep INQOVI and all medicines out of the reach of children.

General information about the safe and effective use of INQOVI

Medicines are sometimes prescribed for purposes other than those listed in a Patient Information leaflet. Do not use INQOVI for a condition for which it was not prescribed. Do not give INQOVI to other people, even if they have the same symptoms that you have. It may harm them. You can ask your pharmacist or healthcare provider for information about INQOVI that is written for health professionals.

What are the ingredients in INQOVI?

Active ingredients: decitabine and cedazuridine

Inactive ingredients: lactose monohydrate, hypromellose, croscarmellose sodium, colloidal silicon dioxide and magnesium stearate. The film coating material contains polyvinyl alcohol, titanium dioxide, polyethylene glycol, talc, and iron oxide red.

Manufactured for: Taiho Pharmaceutical Co., Ltd. Japan
Distributed by: Taiho Oncology, Inc., Princeton, NJ 08540 USA

INQOVI is a registered trademark of Taiho Pharmaceutical Co., Ltd.
For more information, go to www.INQOVI.com or call 1-888-878-2446.

This Patient Information has been approved by the U.S. Food and Drug Administration

Issued: 10/2024

PRINCIPAL DISPLAY PANEL - 35 mg/100 mg Tablet Carton

NDC 64842-0727-9
Rx Only

INQOVI®
(decitabine and cedazuridine) tablets

35 mg/100 mg per tablet

CAUTION: Hazardous Agent

One Blister card
containing 5 tablets

TAIHO
ONCOLOGY, INC.